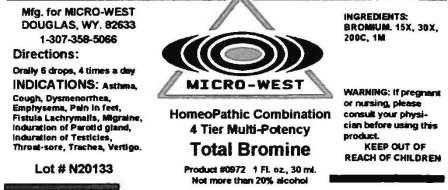 DRUG LABEL: Total Bromine
NDC: 58836-0972 | Form: LIQUID
Manufacturer: White Manufacturing Incorporated
Category: homeopathic | Type: HUMAN OTC DRUG LABEL
Date: 20110729

ACTIVE INGREDIENTS: Bromine 15 [hp_X]/30 mL
INACTIVE INGREDIENTS: ALCOHOL

DRUG FACTS

ACTIVE INGREDIENTS

BROMIUM-15X, 30X, 200C, 1M

USES

ASTHMA, COUGH, PAIN IN FEET, FISTULA LACHRYMALIS, MIGRAINE, INDURATION OF PAROTID GLAND, INDURATION OF TESTICLES, THROAT-SORE, TRACHEA, VERTIGO

KEEP OUT OF REACH OF CHILDREN

INDICATIONS

INDICATIONS: ASTHMA, COUGH, DYSMENORRHEA, EMPHYSEMA, PAIN IN FEET, FISTULA LACHRYMALIS, MIGRAINE, INDURATION OF PAROTID GLAND, INDURATION OF TESTICLES, THROAT-SORE, TRACHEA, VERTIGO

ASK DOCTOR

WARNING: IF PREGNANT OR NURSING, PLEASE CONSULT YOUR PHYSICIAN BEFORE USING THIS PRODUCT

DIRECTIONS

ORALLY, 6 DROPS, 4 TIMES A DAY

INACTIVE INGREDIENT

NOT MORE THAN 20% ALCOHOL

Principal Display Panel Total Bromine Label

test image